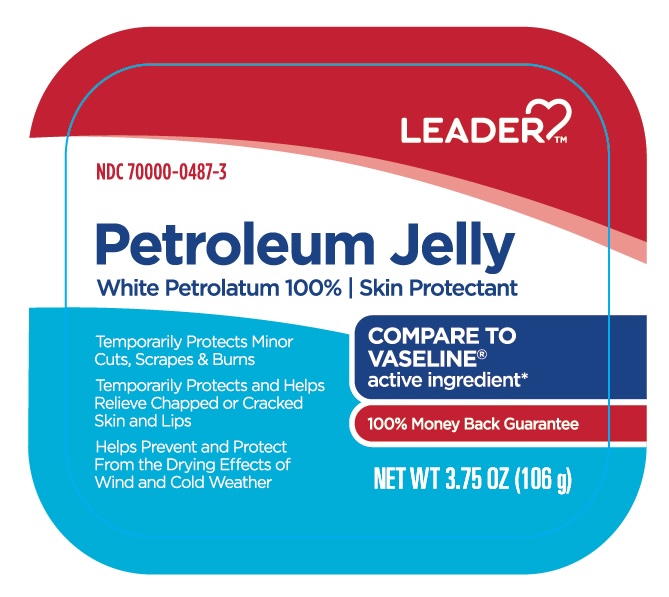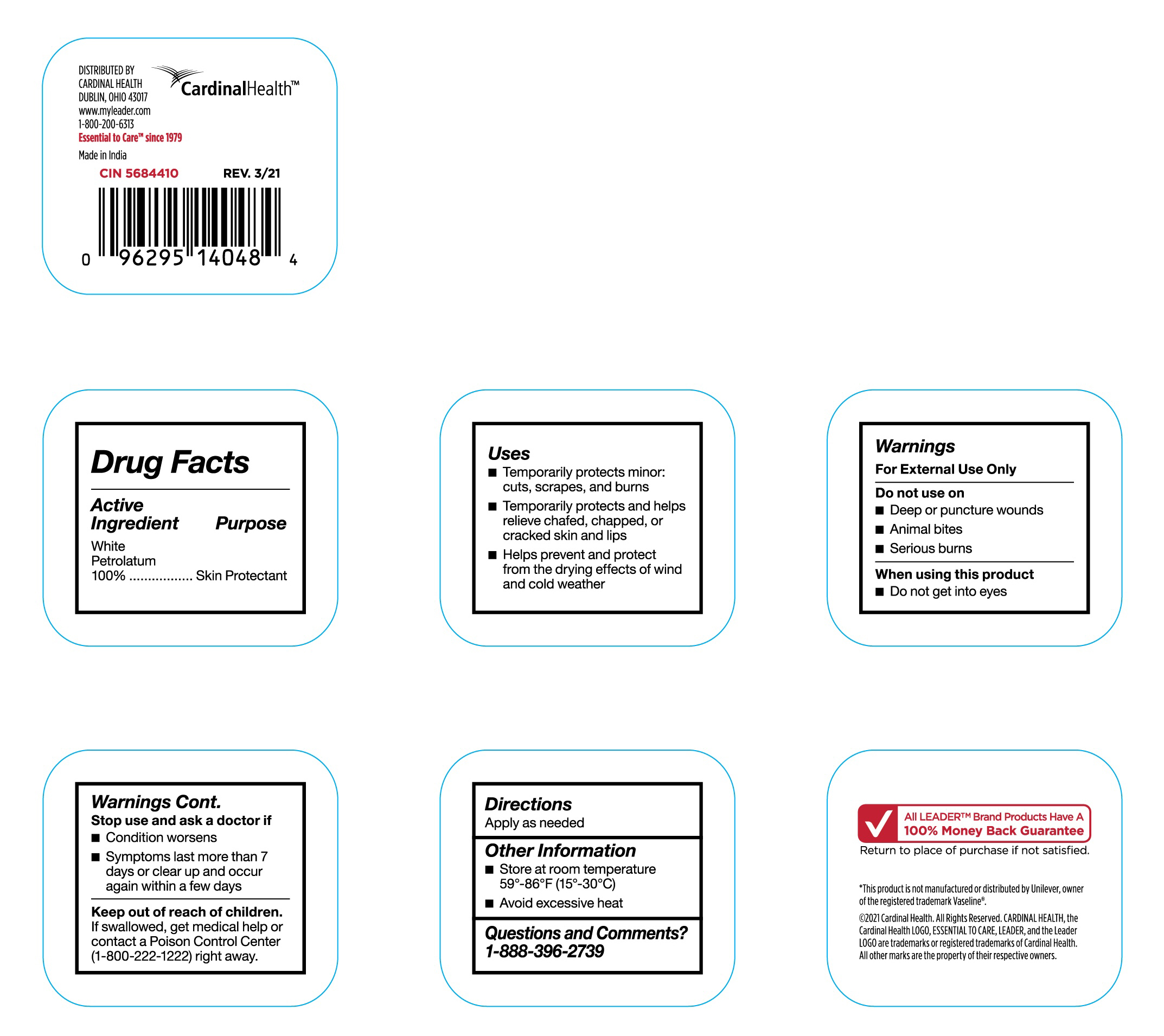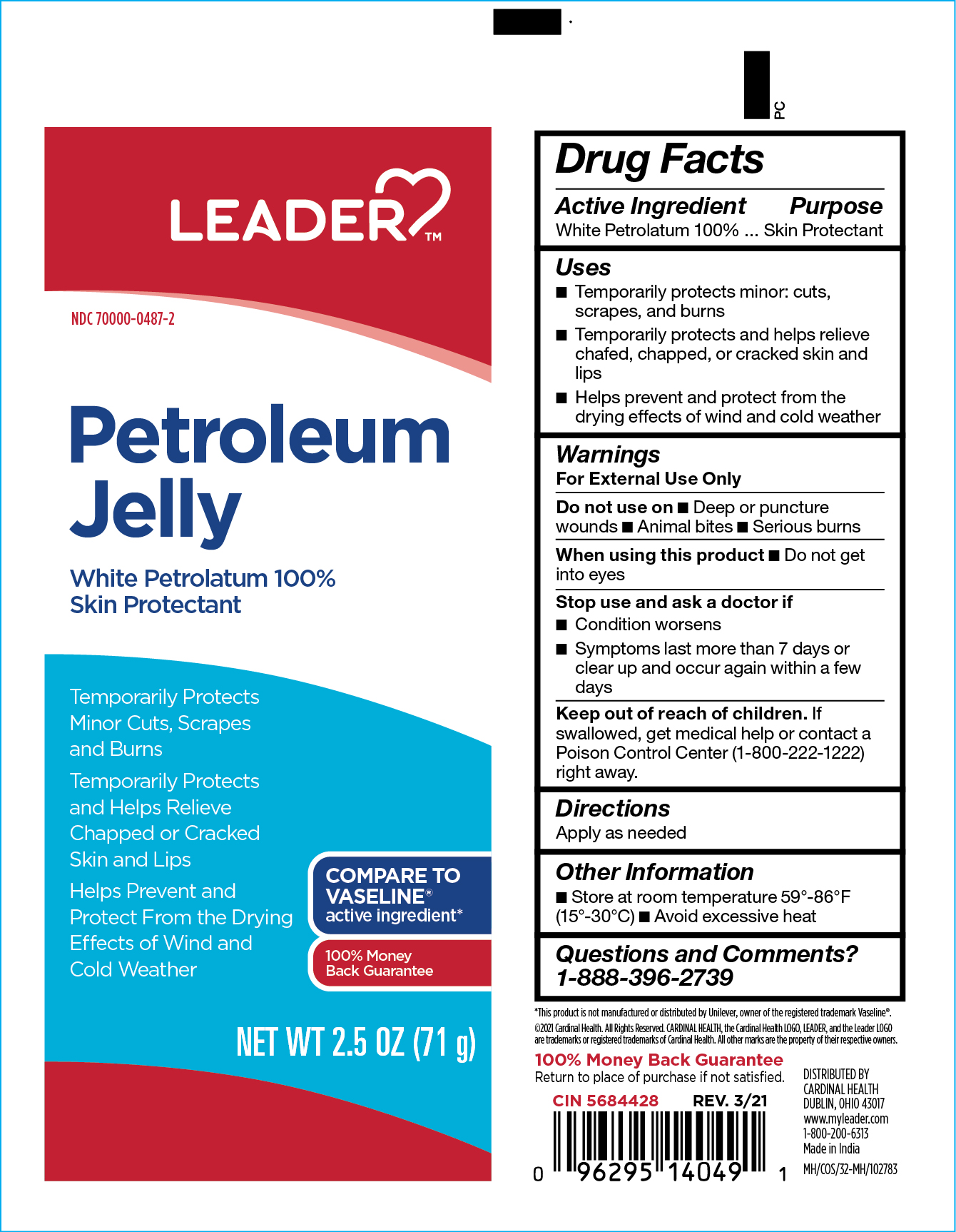 DRUG LABEL: White Petrolatum
NDC: 70000-0487 | Form: OINTMENT
Manufacturer: Cardinal Health
Category: otc | Type: HUMAN OTC DRUG LABEL
Date: 20251126

ACTIVE INGREDIENTS: PETROLATUM 100 g/100 g

CR-5684410 Leader Petroleum Jelly
CR-5684428 Leader Petroleum Jelly

Active Ingredient

White Petrolatum 100%

Purpose

Skin Protectant

Uses

• Temporarily protects minor: cuts, scrapes, and burns

• Temporarily protects and helps relieve chafed, chapped, or cracked skin and lips

• Helps prevent and protect from the drying effects of wind and cold weather

Warnings

For External Use Only

Do not use on

• Deep or puncture wounds

• Animal bites

• Serious burns

When using this product

• Do not get into eyes

Stop use and ask a doctor if

• Condition worsens

• Symptoms last more than 7 days or clear up and occur again within a few days

Keep out of reach of children.

If swallowed, get medical help or contact a Poison Control Center (1-800-222-1222) right away.

Directions

Apply as needed

Other Information

• Store at room temperature 59°-86°F (15°-30°C)

• Avoid excessive heat

Questions and Comments?

1-888-396-2739

Inactive Ingredients

No inactive ingredients

Label

CR-5684428 Label

Label

CR-5684410 IN

Label

CR-5684410 DM